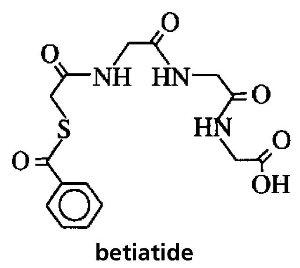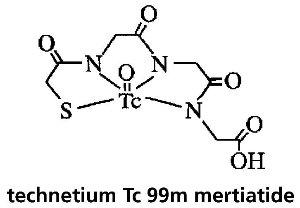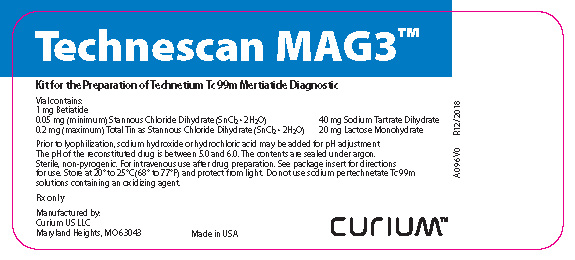 DRUG LABEL: Technescan MAG3
NDC: 69945-096 | Form: INJECTION, POWDER, LYOPHILIZED, FOR SOLUTION
Manufacturer: Curium US LLC
Category: prescription | Type: HUMAN PRESCRIPTION DRUG LABEL
Date: 20260106

ACTIVE INGREDIENTS: BETIATIDE 1 mg/1 1
INACTIVE INGREDIENTS: STANNOUS CHLORIDE 0.05 mg/1 1; STANNOUS CHLORIDE ANHYDROUS 0.2 mg/1 1; SODIUM TARTRATE 40 mg/1 1; LACTOSE MONOHYDRATE 20 mg/1 1; SODIUM HYDROXIDE; HYDROCHLORIC ACID

Technescan MAG3™
Kit for the Preparation of Technetium Tc 99m Mertiatide
Rx only
Diagnostic-For Intravenous Use

DESCRIPTION

Technescan MAG3™ is a kit for the preparation of technetium Tc 99m mertiatide, a diagnostic radiopharmaceutical. It is supplied as a sterile, nonpyrogenic, lyophilized powder. Each vial contains betiatide (N-[N-[N-[(benzoylthio) acetyl]glycyl]glycyl]-glycine). After reconstitution with sterile sodium pertechnetate Tc 99m injection, the technetium Tc 99m mertiatide (disodium[N-[N-[N-(mercaptoacetyl) glycyl]glycyl] glycinato (2-) - N,N′,N″,S′]oxotechnetate (2-)) which is formed is suitable for intravenous administration.

Each 10 milliliter vial contains 1 milligram betiatide, 0.05 milligram (minimum) stannous chloride dihydrate (SnCl2•2H2O) and 0.2 milligram (maximum) total tin expressed as stannous chloride dihydrate (SnCl2•2H2O), 40 milligrams sodium tartrate dihydrate (Na2C4H2O6•2H2O), and 20 milligrams lactose monohydrate. Prior to lyophilization, sodium hydroxide or hydrochloric acid may be added for pH adjustment. The pH of the reconstituted drug is between 5.0 and 6.0. No bacteriostatic preservative is present. The contents are sealed under argon. Betiatide is light sensitive and must be protected from light. Betiatide and technetium Tc 99m mertiatide have the following structural formulas:

PHYSICAL CHARACTERISTICS

Technetium Tc 99m decays by isomeric transition with a physical half-life of 6.02 hours. [Kocher, David C., "Radioactive Decay Tables," DOE/TIC-11026, 108 (1981).] The principal photon that is useful for detection and imaging is listed in Table 1.

Table 1. Principal Radiation Emission Data
Radiation M | Mean % per Disintegration | Energy (keV)
Gamma-2 | 89.07 | 140.5

The specific gamma ray constant for Technetium Tc 99m is 0.78 R/mCi-hr at 1 cm. The first half-value thickness of lead (Pb) for Technetium Tc 99m is 0.017 cm. A range of values for the relative attenuation of the radiation emitted by this radionuclide that results from interposition of various thicknesses of Pb is shown in Table 2. For example, the use of 0.25 cm of Pb will decrease the external radiation exposure by a factor of about 1000.

Table 2. Radiation Attenuation by Lead Shielding
Shield Thickness (Pb) cm | Coefficient of Attenuation
0.017 | 0.5
0.08 | 10^-1
0.16 | 10^-2
0.25 | 10^-3
0.33 | 10^-4

To correct for physical decay of the radionuclide, the fractions that remain at selected time intervals after the time of calibration are shown in Table 3.

Table 3. Physical Decay Chart: Technetium Tc 99m, Half-life 6.02 Hours
Hours | Fraction Remaining | Hours | Fraction Remaining
0* | 1.000 | 7 | 0.447
1 | 0.891 | 8 | 0.398
2 | 0.794 | 9 | 0.355
3 | 0.708 | 10 | 0.316
4 | 0.631 | 11 | 0.282
5 | 0.562 | 12 | 0.251
6 | 0.501
* Calibration Time

CLINICAL PHARMACOLOGY

Following intravenous injection of technetium Tc 99m mertiatide, the appearance, concentration, and excretion of the tracer in the kidney can be monitored to assess renal function. Although technetium Tc 99m mertiatide is highly plasma protein bound following intravenous injection, the protein binding is reversible and the tracer is rapidly excreted by the kidneys via active tubular secretion and glomerular filtration. Following intravenous injection of technetium Tc 99m mertiatide in normal volunteers, 89% of the tracer was plasma protein bound. In healthy subjects with normal renal function (mean serum creatinine 1.2 mg/dL) technetium Tc 99m mertiatide was rapidly cleared from the blood. The plasma clearance was approximately 0.3 liters/minute and the amount of technetium Tc 99m mertiatide excreted in the urine in three hours was nearly 90% of the dose. In a study performed in three patients with renal impairment (serum creatinine greater than 6.3 mg/dL), there was decreased blood clearance and a decrease in the amount excreted in the urine over three hours. In these patients, 78% of the tracer was plasma protein bound after intravenous injection. The mean plasma clearance of technetium Tc 99m mertiatide was 0.03 liters/minute and 21.3% was excreted in three hours on average. In both healthy subjects and patients with renal impairment, the plasma concentration-time profile showed a biexponential decline.

INDICATIONS AND USAGE

Technetium Tc 99m mertiatide is a renal imaging agent for use in the diagnosis of congenital and acquired abnormalities, renal failure, urinary tract obstruction, and calculi in adults and pediatric patients. (See Pediatric Use.) It is a diagnostic aid in providing renal function, split function, renal angiograms, and renogram curves for whole kidney and renal cortex.

CONTRAINDICATIONS

None known.

WARNINGS

None known.

PRECAUTIONS

General

1. The contents of this kit are not radioactive. However, after sodium pertechnetate Tc 99m is added, adequate shielding of the final preparation must be maintained.
2. Contents of the reaction vial are intended only for use in the preparation of technetium Tc 99m mertiatide and are NOT to be administered directly to the patient.
3. To help reduce the radiation dose to the bladder, as well as other target organs, the patient should increase his or her fluid intake (unless medically contraindicated) and void as often as possible after the injection of technetium Tc 99m mertiatide for six hours after the imaging procedure.
4. Technetium Tc 99m mertiatide should not be used more than six hours after preparation.
5. The components of the kit are sterile and nonpyrogenic. It is essential that the user follow the directions carefully and use aseptic procedures normally employed in making additions and withdrawals from sterile, nonpyrogenic containers during the addition of pertechnetate solution and the withdrawal of doses for patient administration.
6. The technetium Tc 99m labeling reactions involved in preparing Technescan MAG3 depend on maintaining the stannous ion in the reduced state. Any oxidant present in the sodium pertechnetate Tc 99m may adversely affect the quality of the radiopharmaceutical. Therefore, sodium pertechnetate Tc 99m containing oxidants should not be employed.
7. As in the use of any other radioactive material, care should be taken to ensure minimum radiation exposure to the patient and to occupational workers.
8. Radiopharmaceuticals should be used only by physicians who are qualified by specific training in the safe use and handling of radionuclides.

Carcinogenesis, Mutagenesis, Impairment of Fertility

No long term animal studies have been performed to evaluate carcinogenic or mutagenic potential, or whether this drug affects fertility in males or females.

Pregnancy

Animal reproduction studies have not been conducted with technetium Tc 99m mertiatide. It is also not known whether this drug can cause fetal harm when administered to a pregnant woman or can affect reproduction capacity. Technetium Tc 99m mertiatide should be given to a pregnant woman only if clearly needed.

Nursing Mothers

Technetium Tc 99m is excreted in human milk during lactation, therefore, formula feedings should be substituted for breast feeding.

Pediatric Use

Safety and effectiveness in pediatric patients under the age of 30 days have not been established.

ADVERSE REACTIONS

The following adverse reactions have been reported: nausea, vomiting, wheezing, dyspnea, itching, rash, tachycardia, hypertension, shaking chills, fever, and seizure.

DOSAGE AND ADMINISTRATION

The suggested dose range employed in the average adult patient (70 kg) for renal function and imaging studies is 185 MBq (5 mCi) to 370 MBq (10 mCi). In pediatric patients the recommended dose range is 2.6 MBq/kg (70 μCi/kg) to 5.2 MBq/kg (140 μCi/kg) with a minimum dose of 37 MBq (1 mCi).

The patient dose should be measured by a suitable radioactivity calibration system immediately prior to administration.

Parenteral drug products should be inspected visually for particulate matter and discoloration prior to administration.

Aseptic procedures and a shielded syringe should be employed in withdrawing doses for administration to patients. The user should wear waterproof gloves during the administration procedure.

RADIATION DOSIMETRY

The estimated absorbed radiation doses from an intravenous administration of technetium Tc 99m mertiatide are presented in Table 4.

HOW SUPPLIED

Catalog Number 096.

Technescan MAG3 is supplied as a lyophilized powder packaged in vials. Each reaction vial contains 1 mg betiatide, 0.05 mg (minimum) stannous chloride dihydrate (SnCl2•2H2O), 0.2 mg (maximum) total tin expressed as stannous chloride dihydrate (SnCl2•2H2O), 40 mg sodium tartrate dihydrate (Na2C4H2O6•2H2O), and 20 mg lactose monohydrate.

The pH of the reconstituted drug is between 5.0 and 6.0. No bacteriostatic preservative is present.

Packages containing 5 reaction vials (NDC 69945-096-20) are available.

STORAGE

Technescan MAG3 should be stored at controlled room temperature 20° to 25°C (68° to 77°F) and protected from light until use. The reconstituted vial should be stored at room temperature (15° to 30°C) and must be used within six hours of preparation.

Table 4. Radiation Dose Estimates for Tc 99m Mertiatide
 | 8-day Old |  | 1-year Old** |  | 5-year Old** |  | 10-year Old** |  | 15-year Old |  | Adult
Assumed Weight (kg) | 3.4 |  | 9.8 |  | 19 |  | 32 |  | 57 |  | 70
Tc 99m Mertiatide Dose | 37 MBq (1 mCi) |  | 72.52 MBq (1.96 mCi) |  | 140.6 MBq (3.8 mCi) |  | 236.8 MBq (6.4 mCi) |  | 370 MBq (10 mCi) |  | 370 MBq (10 mCi)
Organ | mSv | rem | mSv | rem | mSv | rem | mSv | rem | mSv | rem | mSv | rem
Gallbladder Wall | 2.701 | 0.27 | 2.466 | 0.235 | 1.547 | 0.160 | 1.658 | 0.166 | 1.961 | 0.200 | 1.628 | 0.160
Lower Large Intestine Wall | 1.739 | 0.17 | 1.595 | 0.161 | 2.250 | 0.220 | 2.368 | 0.237 | 4.070 | 0.400 | 3.256 | 0.330
Small Intestine | 0.518 | 0.052 | 0.5439 | 0.055 | 1.195 | 0.122 | 1.397 | 0.141 | 2.035 | 0.200 | 1.628 | 0.160
Upper Large Intestine Wall | 0.962 | 0.096 | 0.943 | 0.096 | 1.828 | 0.186 | 2.0365 | 0.205 | 2.442 | 0.250 | 1.887 | 0.190
Kidneys | 1.406 | 0.14 | 1.088 | 0.112 | 1.308 | 0.129 | 1.5155 | 0.154 | 1.739 | 0.180 | 1.443 | 0.140
Liver | 0.3219 | 0.032 | 0.3046 | 0.031 | 0.394 | 0.038 | 0.4262 | 0.0435 | 0.481 | 0.048 | 0.3626 | 0.036
Ovaries | 0.592 | 0.058 | 0.6164 | 0.061 | 1.322 | 0.133 | 1.5392 | 0.154 | 3.330 | 0.330 | 2.5900 | 0.260
Red Marrow | 0.1628 | 0.016 | 0.1595 | 0.0161 | 0.281 | 0.0277 | 0.3552 | 0.0352 | 0.629 | 0.063 | 0.4810 | 0.050
Testes | 0.518 | 0.051 | 0.5294 | 0.053 | 1.0826 | 0.110 | 1.1840 | 0.122 | 2.368 | 0.240 | 1.628 | 0.160
Urinary Bladder Wall | 11.470 | 1.1 | 9.428 | 0.921 | 21.090 | 2.090 | 23.680 | 2.368 | 59.20 | 6.00 | 48.1000 | 4.80
Total Body | 0.2405 | 0.024 | 0.2176 | 0.022 | 0.3656 | 0.0365 | 0.4026 | 0.0410 | 0.814 | 0.081 | 0.6660 | 0.065
*Calculated by Oak Ridge Associated Universities, based upon the pediatric phantom series of Christy and Eckerman of Oak Ridge National Laboratories. The adult radiation absorbed doses were calculated based on data from ten normal volunteers using the Medical Internal Radiation Dose Committee (MIRD) schema.
**Radioactive doses for 1-, 5-, and 10-year olds are based on a maximum dose of 7.4 MBq/kg (200 μCi/kg).

INSTRUCTIONS FOR THE PREPARATION OF TECHNETIUM Tc 99m MERTIATIDE

Note:Read complete directions thoroughly before starting preparation procedure.

Procedural Precautions and Notes

1. Solutions of sodium pertechnetate Tc 99m which contain oxidizing agents (i.e., sodium hypochlorite or hydrogen peroxide) should not be used.
  NOTE:Do not use Tc 99m eluate more than 6 hours after its elution from the generator.
2. All transfers and vial stopper entries must be done using aseptic technique.
3. The water bath used for heating the contents of the reaction vial must be at a continuous rolling boil during the heating step of the preparation procedure. The vial should be in direct contact with the rolling boil water of the bath, and the level of the bath must be at least even with the level of the contents of the vial.
4. The temperature of a lead incubation shield should be allowed to reach the temperature of the water bath before incubating the reaction vial. The shield should be designed so that water flows through the interior of the shield.

Note 1:Wear waterproof gloves during the entire preparation procedure and during subsequent patient dose withdrawals from the reaction vial.

Note 2:Make all transfers of sodium pertechnetate Tc 99m solution during the preparation procedure with an adequately shielded syringe.

Note 3:Keep the radioactive preparation in the lead shield described below (with cap in place) during the useful life of the radioactive preparation. Maintain adequate shielding during the life of the product and use a shielded, sterile syringe for withdrawing and injecting the preparation.

Procedure for the Preparation of Technetium Tc 99m Mertiatide

1. Prepare a rolling boil water bath containing a vial shield with openings cut in it to allow the water to circulate through the shield. The openings should be oriented to prevent radiation leakage.
2. Place the reaction vial in a lead dispensing shield fitted with a lid and with a minimum wall thickness of 1/8 inch.
3. Swab the rubber stopper of the reaction vial with an appropriate antiseptic. Insert a filter-containing venting needle (provided) through the vial stopper. Inject 4 to 10 milliliters of sodium pertechnetate Tc 99m solution containing 740 megabecquerels (20 mCi) to 3.70 gigabecquerels (100 mCi) into the vial. If required, use nonbacteriostatic normal saline to dilute the sodium pertechnetate Tc 99m solution to the desired concentration prior to addition to the vial.
  NOTE:Make sure the water bath is at boiling temperature before adding sodium pertechnetate Tc 99m to the reaction vial.
4. Immediately following the addition of sodium pertechnetate Tc 99m solution to the reaction vial, withdraw the syringe plunger to a volume of 2 mL, thus removing 2 mL of argon gas and adding 2 mL of filtered air to the vial. The air is required to oxidize excess stannous ion. Remove both needles from the vial.
  NOTE: The addition of 2 mL air is required to prevent the progressive formation of technetium Tc 99m labeled impurities.
5. Invert the reaction vial several times to obtain complete mixing.
6. Immediately transfer the reaction vial to the water bath. Place it inside the lead shield which has been equilibrated to the temperature of the boiling water bath. Allow the reaction vial to incubate for 10 minutes.
  NOTE: The reaction vial MUSTbe placed in the boiling water bath within 5 minutes of the addition of sodium pertechnetate Tc 99m solution.
7. Remove the reaction vial from the boiling water bath and place in the lead dispensing shield. Allow the contents of the vial to cool for approximately 15 minutes to reach body temperature. Using proper shielding, the vial contents should be visually inspected.
  The solution should be clear and free of particulate matter. If not, the preparation should not be used.
8. Assay the reaction vial using a suitable radioactivity calibration system. Record the date, time, total technetium Tc 99m activity, volume, and technetium Tc 99m concentration on the radioassay information label and affix the label to the lead dispensing shield.
9. The radiochemical purity of the reconstituted solution must be checked prior to administration to the patient. If the radiochemical purity is less than 90%, the product must not beused.
10. Store the reaction vial containing the technetium Tc 99m mertiatide at room temperature (15° to 30°C) until use. The technetium Tc 99m mertiatide preparation must be used within six hours of preparation.

RECOMMENDED METHOD FOR DETERMINATION OF RADIOCHEMICAL PURITY OF Technescan MAG3™

Required Materials:

Waters Sep-Pak™ C18 Cartridges, Part #51910,
200 proof ethanol
0.9% Sodium Chloride Injection, USP
0.001N hydrochloric acid*
1:1 ethanol/saline solution**
Disposable syringes:
10 mL, no needle required
1 mL, with needle
Disposable culture tubes or vials, minimum 15 mL capacity
Ion chamber for measurement of radioactive samples.

*May be prepared by diluting 1 mL of 0.10N hydrochloric acid to 100 mL with Water for Injection, USP, or by other appropriate dilution of more concentrated hydrochloric acid. For example, 0.1 mL of 36% (~11.6N) hydrochloric acid diluted to a total volume of 1,150 mL.

**Prepared by mixing equal volumes of the 200 proof ethanol and 0.9% Sodium Chloride Injection, USP.

Preparation of Sep-Pak Cartridge

1. Using a 10 mL syringe, push 10 mL of 200 proof ethanol through the Sep-Pak cartridge. Discard the eluate.
2. Similarly, flush the cartridge with 10 mL of the 0.001N hydrochloric acid. Discard the eluate.
3. Drain the cartridge by pushing 5 mL of air through the cartridge with the syringe. Discard the eluate.

Sample Analysis

1. Apply 0.1 mL of the technetium Tc 99m mertiatide preparation to the head of the cartridge through the longer end of the cartridge using a 1 mL syringe with needle.
  Note:The cartridge and all solutions eluted from it will be radioactive after this step.
2. With a disposable 10 mL syringe, slowly push 10 mL of 0.001N hydrochloric acid through the cartridge. Collect this fraction in a culture tube or vial for counting.
3. Similarly, elute the cartridge with 10 mL of the 1:1 ethanol/saline solution. Be sure that this solution is pushed through the cartridge slowly so that the elution occurs in a drop-wise manner. Collect this 10 mL fraction in a second culture tube or vial for counting.
4. Place the Sep-Pak cartridge in a third culture tube or vial for counting.

Counting

1. Assay the activity of the first sample elution in an ion chamber. This fraction contains the hydrophilic impurities (free pertechnetate, technetium tartrate, etc.) and a fraction of reduced-hydrolyzed technetium.
2. Assay the activity of the second elution. This fraction contains the technetium Tc 99m mertiatide complex.
3. Assay the activity of the Sep-Pak cartridge in the third culture tube or vial. This component contains the remaining reduced-hydrolyzed technetium and non-elutable impurities.

Calculations

1. Percent technetium Tc 99m mertiatide =

Activity of 2nd (ethanol/saline) fraction | x 100%
Total activity of all three fractions | x 100%

2. Percent hydrophilic impurities =

Activity of 1st (0.001N HCl acid) fraction | x 100%
Total activity of all three fractions | x 100%

3. Percent non-elutable impurities =

Activity remaining on Sep-Pak cartridge | x 100%
Total activity of all three fractions | x 100%

This reagent kit is approved for distribution to persons licensed by the U.S. Nuclear Regulatory Commission to use byproduct material identified in Section 35.200 or under an equivalent license of an Agreement State.

©2025 Curium US LLC. Technescan MAG3TM, CuriumTM, and the Curium logo are trademarks of a Curium company.

Sep-Pak is a trademark of Waters Technologies Corporation.

Manufactured by:
Curium US LLC
2703 Wagner Place
Maryland Heights, MO 63043

Made in USA

A096I0

R03/2025

CURIUMTM

PRINCIPAL PANEL DISPLAY - A096V0

Technescan MAG3™

Kit for the Preparation of Technetium Tc 99m Mertiatide Diagnostic

Vial contains:
1 mg Betiatide
0.05 mg (minimum) Stannous Chloride Dihydrate (SnCl2● 2H2O)
40 mg Sodium Tartrate Dihydrate
0.2 mg (maximum) Total Tin as Stannous Chloride Dihydrate (SnCl2● 2H2O)
20 mg Lactose Monohydrate

Prior to lyophilization, sodium hydroxide or hydrochloric acid may be added for pH adjustment. The pH of the reconstituted drug is between 5.0 and 6.0. The contents are sealed under argon. Sterile, non-pyrogenic. For intravenous use after drug preparation. See package insert for directions for use. Store at 20˚ to 25˚C (68˚ to77˚F) and protect from light. Do not use sodium pertechnetate Tc 99m solutions containing an oxidizing agent.

Rx only

Manufactured by:
Curium US LLC
Maryland Heights, MO 63043

Made in USA

CURIUMTM

A096V0

R12/2018